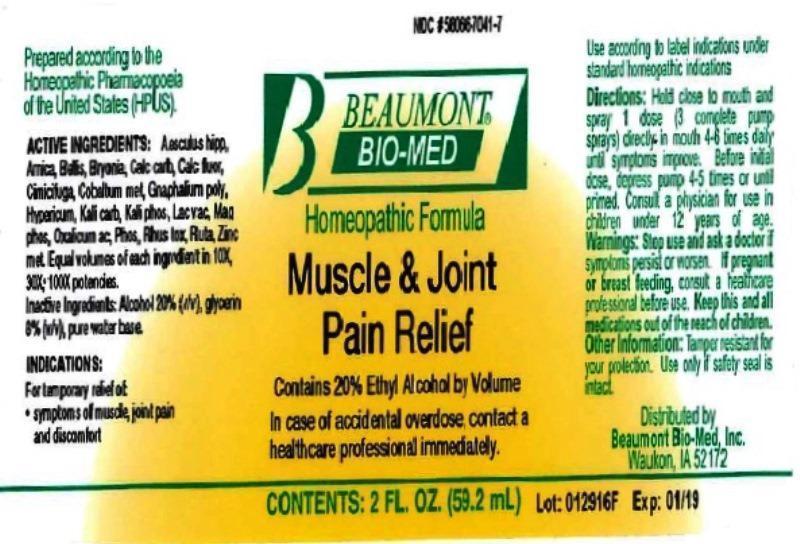 DRUG LABEL: Muscle and Joint Pain Relief
NDC: 58066-7041 | Form: LIQUID
Manufacturer: Beaumont Bio Med
Category: homeopathic | Type: HUMAN OTC DRUG LABEL
Date: 20160909

ACTIVE INGREDIENTS: HORSE CHESTNUT 10 [hp_X]/59.2 mL; ARNICA MONTANA 10 [hp_X]/59.2 mL; BELLIS PERENNIS 10 [hp_X]/59.2 mL; BRYONIA ALBA ROOT 10 [hp_X]/59.2 mL; OYSTER SHELL CALCIUM CARBONATE, CRUDE 10 [hp_X]/59.2 mL; CALCIUM FLUORIDE 10 [hp_X]/59.2 mL; BLACK COHOSH 10 [hp_X]/59.2 mL; COBALT 10 [hp_X]/59.2 mL; PSEUDOGNAPHALIUM OBTUSIFOLIUM 10 [hp_X]/59.2 mL; HYPERICUM PERFORATUM 10 [hp_X]/59.2 mL; POTASSIUM CARBONATE 10 [hp_X]/59.2 mL; POTASSIUM PHOSPHATE, DIBASIC 10 [hp_X]/59.2 mL; COW MILK 10 [hp_X]/59.2 mL; MAGNESIUM PHOSPHATE, DIBASIC TRIHYDRATE 10 [hp_X]/59.2 mL; OXALIC ACID DIHYDRATE 10 [hp_X]/59.2 mL; PHOSPHORUS 10 [hp_X]/59.2 mL; TOXICODENDRON PUBESCENS LEAF 10 [hp_X]/59.2 mL; RUTA GRAVEOLENS FLOWERING TOP 10 [hp_X]/59.2 mL; ZINC 10 [hp_X]/59.2 mL
INACTIVE INGREDIENTS: ALCOHOL; GLYCERIN; WATER

Muscle and Joint Pain Relief

ACTIVE INGREDIENT

HPUS active ingredients: Aesculus hippocastanum, Arnica montana, Bellis perennis, Bryonia, Calcarea carbonica, Calcarea fluorica, Cimicifuga racemosa, Cobaltum metallicum, Gnaphalium polycephalum, Hypericum perforatum, Kali carbonicum, Kali phosphoricum, Lac vaccinum, Magnesia phosphorica, Oxalicum acidum, Phosphorus, Rhus toxicodendron, Ruta graveolens, Zincum metallicum. Equal volumes of each ingredient in 10X, 30X, 100X potencies.

INACTIVE INGREDIENT

Inactive Ingredients: Alcohol @ 20% (v/v), Glycerin @ 8% (v/v), in a pure water base.

INDICATIONS AND USAGE

Indications: For temporary relief of: symptoms of muscle, joint pain and discomfort.

Directions:

- Hold close to mouth and spray 1 dose (3 complete pump sprays) directly in mouth 4-6 times daily until symptoms improve.
- Before initial dose, depress pump 4-5 times or until primed.
- Consult a physician for use in children under 12 years of age.

Use according to label indications and/or standard homeopathic indications.

WARNINGS

Warnings: Stop use and ask a doctor if symptoms persist or worsen. If pregnant or breast feeding, consult a healthcare professional.

KEEP OUT OF REACH OF CHILDREN

- Keep this and all medications out of the reach of children.

Other information: Tamper resistant for your protection. Use only if safety seal is intact.

PURPOSE

For temporary relief of:

- symptoms of muscle, joint pain and discomfort